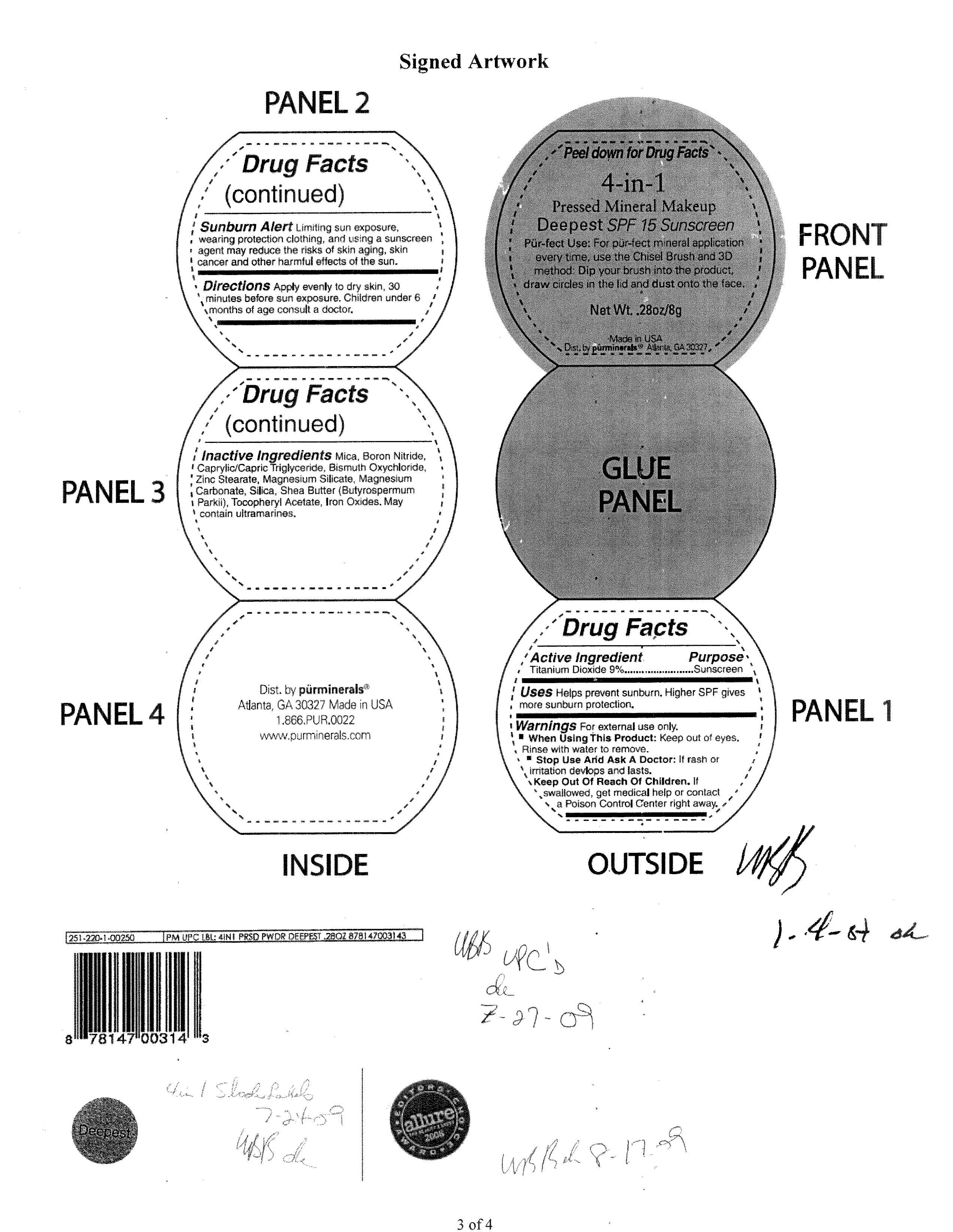 DRUG LABEL: Purminerals  4 in 1 Makeup SPF 15 Deepest
NDC: 67345-0701 | Form: POWDER
Manufacturer: PUR MINERALS
Category: otc | Type: HUMAN OTC DRUG LABEL
Date: 20110422

ACTIVE INGREDIENTS: Titanium Dioxide 0.72 g/8 g
INACTIVE INGREDIENTS: Mica; Boron Nitride; MEDIUM-CHAIN TRIGLYCERIDES; Bismuth Oxychloride; Zinc Stearate; Magnesium Silicate; MAGNESIUM CARBONATE; SILICON DIOXIDE; Shea Butter; Acetate Ion; Iron

Active Ingredient : Titanium Dioxide 9 %

Purpose : Sunscreen

Stop Use and Ask a Doctor : If rash or irritation develops and lasts.

Keep Out of Reach of Children . If swallowed , get medical help or contact a Poison Control Center right away.

INACTIVE INGREDIENT

Inactive Ingredients : Mica , Boron Nitride , Caprylic/Capric Triglyceride , Bismuth Oxychloride , Zinc Stearate , Magnesium Silicate , Magnesium Carbonate , Silica , Shea Butter (Butyrospermum Parkii) , Tocopheryl Acetate , Iron oxide , May contain ultramarines.